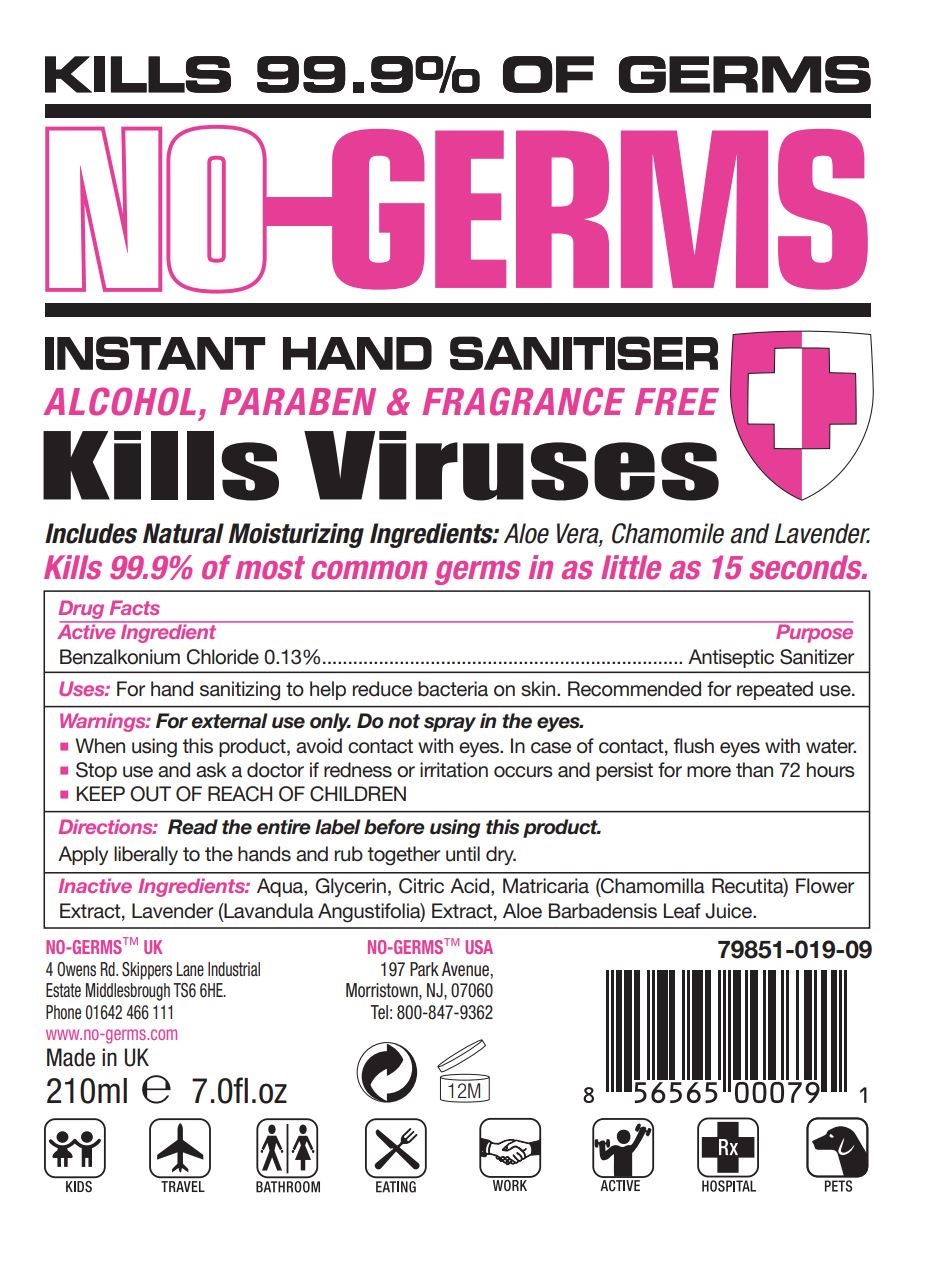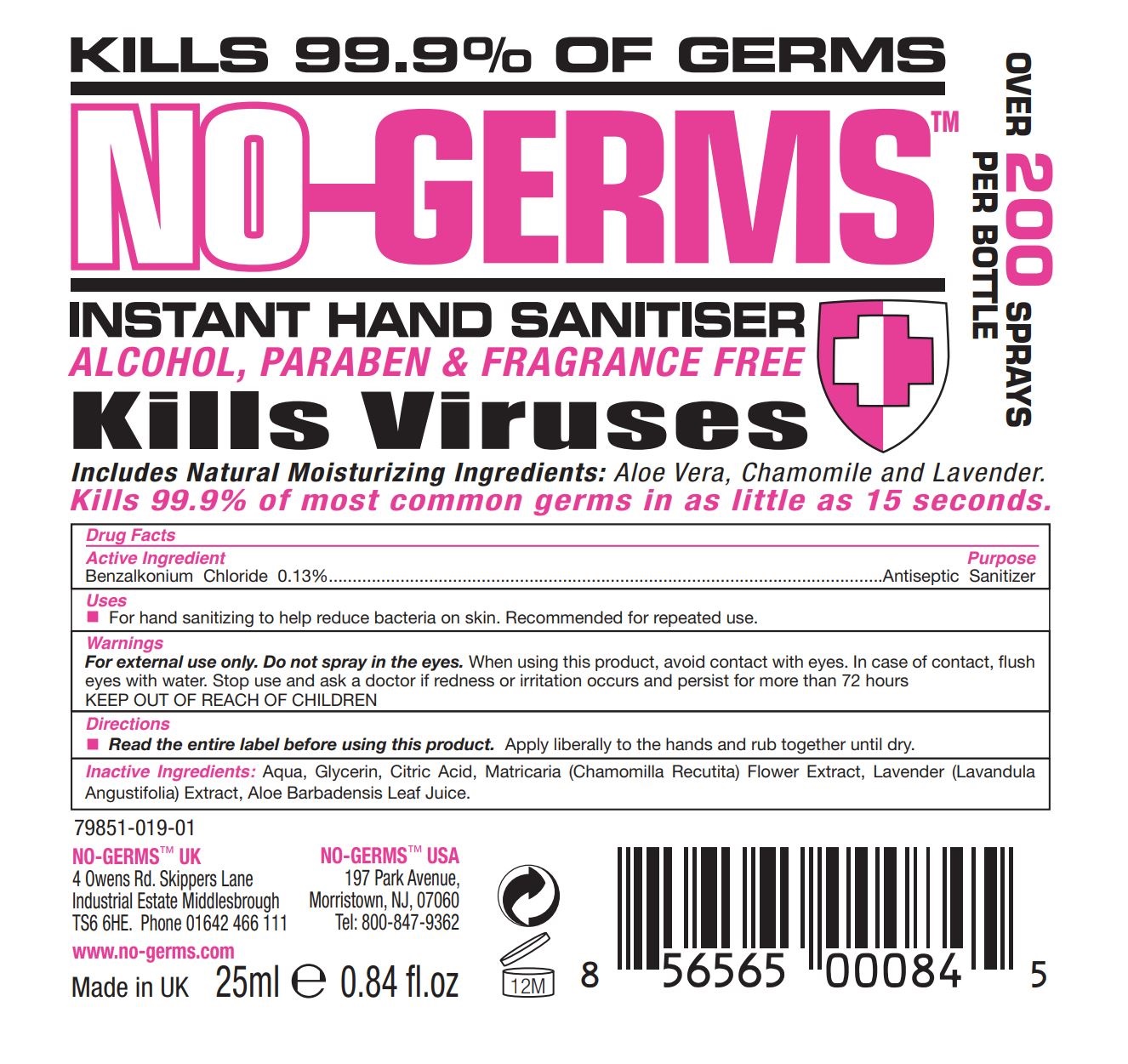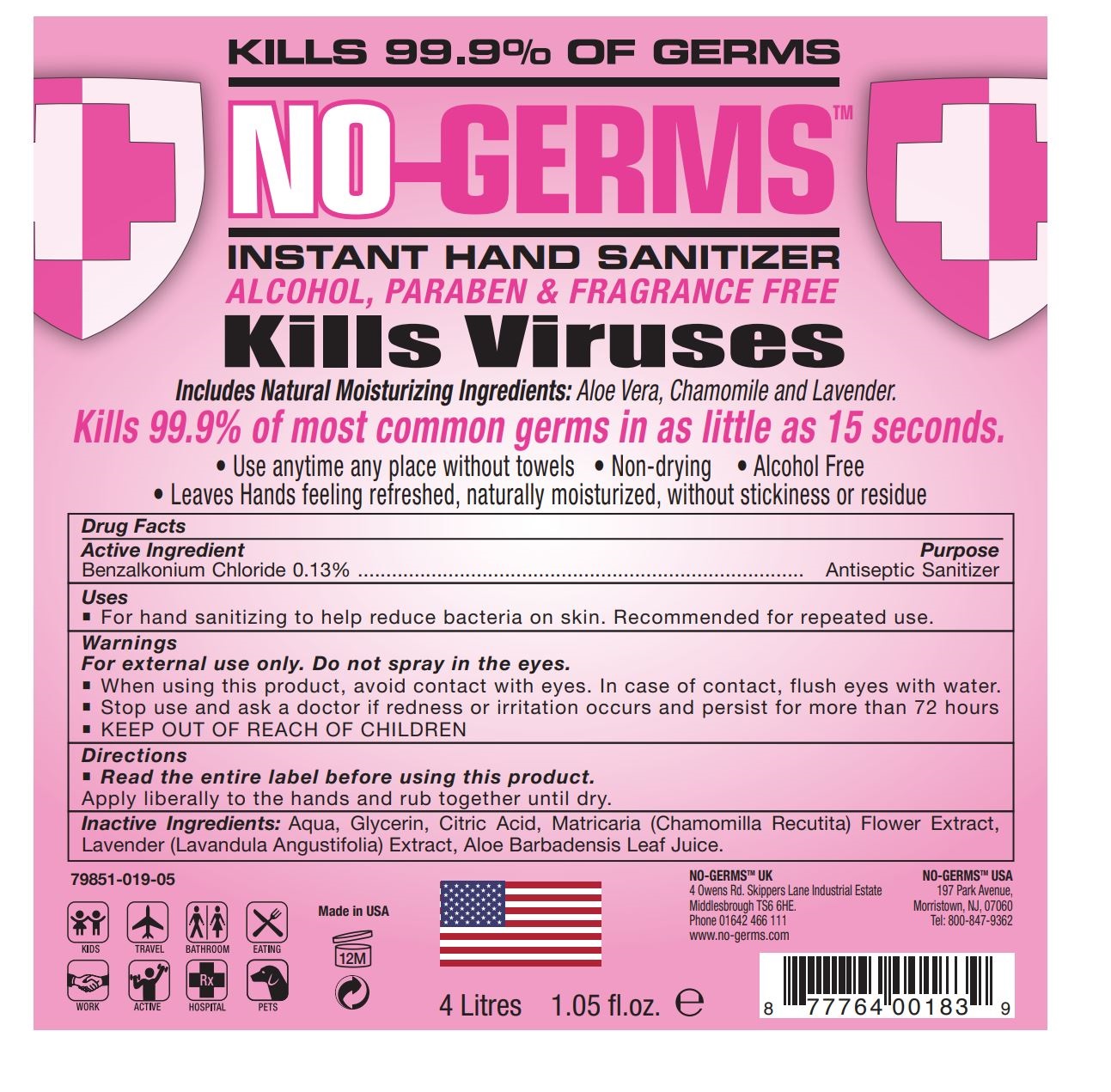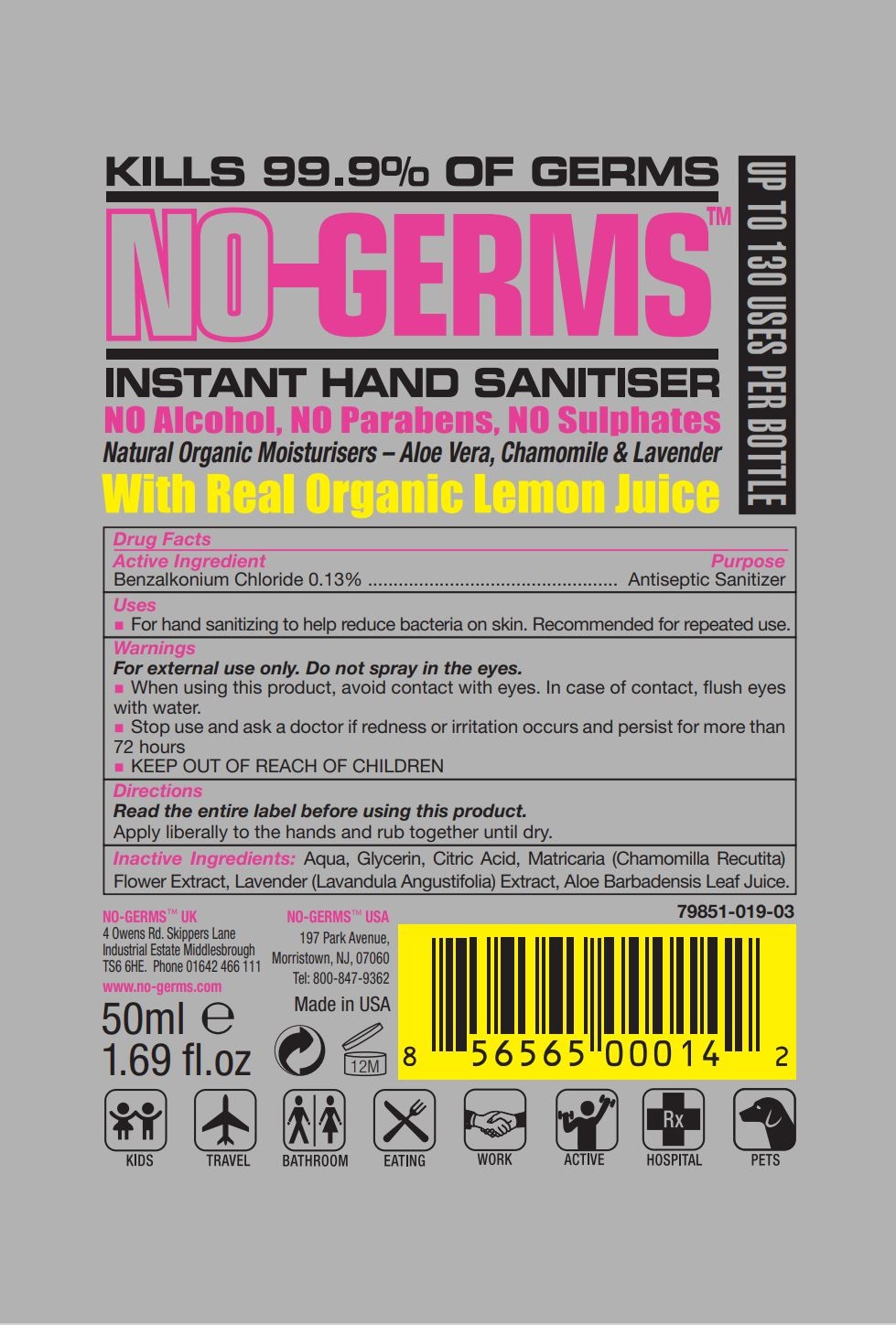 DRUG LABEL: NO-GERMS Hand Sanitizer
NDC: 79851-019 | Form: LIQUID
Manufacturer: Millennium Research USA LLC
Category: otc | Type: HUMAN OTC DRUG LABEL
Date: 20200716

ACTIVE INGREDIENTS: BENZALKONIUM CHLORIDE 0.13 g/100 mL
INACTIVE INGREDIENTS: WATER; CITRIC ACID ACETATE; MATRICARIA CHAMOMILLA; LAVENDER OIL; ALOE VERA LEAF

Active Ingredient

Benzalkonium Chloride 0.13%

Purpose

Antiseptic Sanitizer

Use

For hand sanitizing to help reduce bacteria on skin. Recommended for repeated use.

Warnings

For external use only. Do not spray in the eyes.

- When using this product, avoid contact with eyes. In case of contact, flush eyes with water.
- Stop use and ask a doctor if redness or irritation occurs and persist for more than 72 hours
- KEEP OUT OF REACH OF CHILDREN

KEEP OUT OF REACH OF CHILDREN

Children should be supervised when using this product.

Directions

Read the entire label before using this product.

Apply liberally to the hands and rub together until dry.

Inactive Ingredients

Aqua, Glycerin, Citric Acid, Matricaria (Chamomilla Recutita) Flower Extract, Lavender (Lavandula Angustifolia) Extract, Aloe Barbadensis Leaf Juice